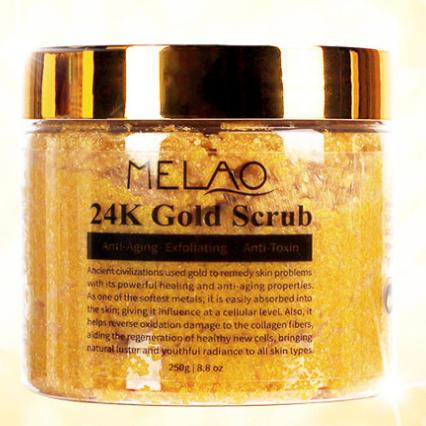 DRUG LABEL: MELAO 24K Gold Scrub
NDC: 83566-586 | Form: STICK
Manufacturer: Guangzhou Yilong Cosmetics Co., Ltd
Category: otc | Type: HUMAN OTC DRUG LABEL
Date: 20240827

ACTIVE INGREDIENTS: BUTYLENE GLYCOL 3.6 g/100 g
INACTIVE INGREDIENTS: XANTHAN GUM 7 g/100 g; ALLANTOIN 29 g/100 g; PAEONIA ANOMALA WHOLE 3.7 g/100 g; SELENICEREUS GRANDIFLORUS FLOWER 5 g/100 g; GOLD SELENATE 0.7 g/100 g; GLYCERIN 4 g/100 g; .ALPHA.-TOCOPHEROL ACETATE 2 g/100 g; FOSFRUCTOSE 29 g/100 g; AMINO ACIDS, CORN GLUTEN 16 g/100 g

MELAO 24K Gold Scrub

Active ingredients

Butylene Glycol 3.60%

Inactive ingredients

Fructose 29%

Allantoin 29%

Corn Gluten Amino Acids 16%

Xanthan Gum 7%

Cereus Grandiflorus (Cactus) Flower Extract 5%

Glycerin 4%

Paeonia Albiflora Root Extract 3.70%

Gold 0.70%

Tocopherol 2%

Purpose

Remove the aging stratum corneum

Uses

Step 1: Clean and thoroughly dry your skin.
Step 2: Take out the scrub and apply it to the skin.
Step 3: Rub back and forth, then rinse with clean water

Warning

.For external use only.

Stop use and ask a doctor if

rash occurs.

Do not use

on damaged or broken skin.

When using this product

keep out of eyes. Rinse withwater to remove.

Keep out of reach of children.

If swallowed, get medical help or contact a Poison Control Center right away.

DOSAGE & ADMINISTRATION

Squeeze out an appropriate amount of sunscreen and spread evenly on skin.